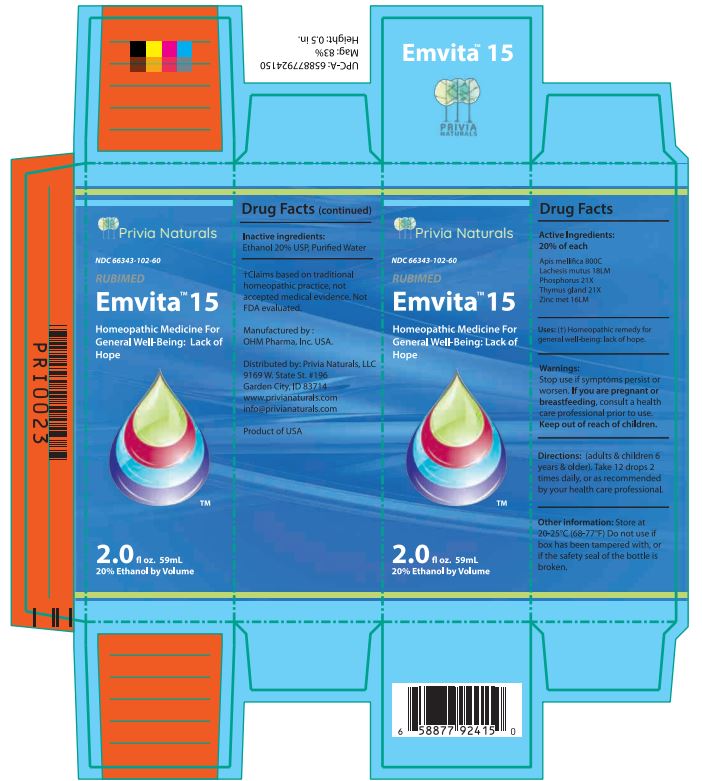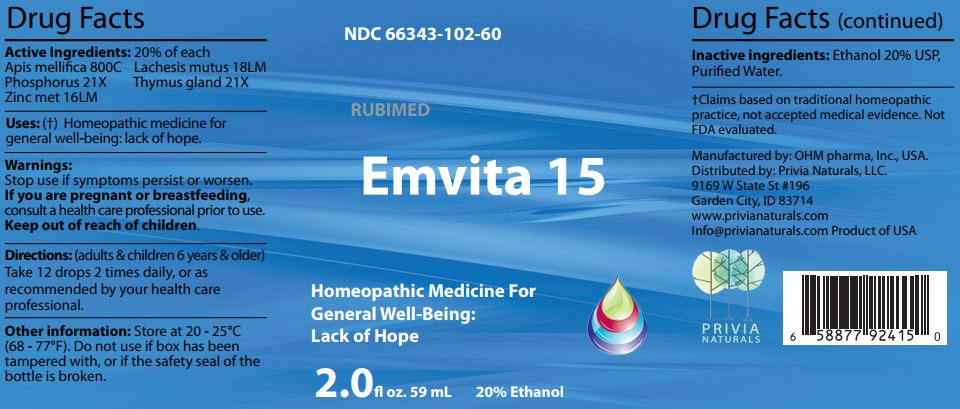 DRUG LABEL: Emvita 15
NDC: 66343-102 | Form: LIQUID
Manufacturer: RUBIMED AG
Category: homeopathic | Type: HUMAN OTC DRUG LABEL
Date: 20241029

ACTIVE INGREDIENTS: APIS MELLIFERA 800 [hp_C]/60 mL; LACHESIS MUTA VENOM 18 [hp_M]/60 mL; PHOSPHORUS 21 [hp_X]/60 mL; BOS TAURUS THYMUS 21 [hp_X]/60 mL; ZINC 16 [hp_M]/60 mL
INACTIVE INGREDIENTS: ALCOHOL; WATER

Emvita 15

Drug Facts Active Ingredients: (HPUS*) 20% of each

Apis mellifica 800C Lachesis mutus 18LM
Phosphorus 21X Thymus gland 21X
Zinc met 16LM

*The letters "HPUS" indicate that the components in this product are officially monographed in the Homeopathic Pharmacopoeia of the United States. †Claims based on traditional homeopathic practice, not accepted medical evidence. Not FDA evaluated.

INDICATIONS AND USAGE

Uses: (†) Homeopathic remedy for general well being: lack of hope.

Warnings:

Stop use if symptoms persist or worsen.

If you are pregnant or breastfeeding,consult a healthcare professional prior to use.

Keep out of reach of children.

DOSAGE AND ADMINISTRATION

Directions: (adults & children 6 years & older)

Take 12 drops 2 times daily, or as recommended by your health care professional.

Other information: Store at 20 - 25°C

(68 - 77°F.) Do not use if box has been

tampered with, or if the safety seal of the

bottle is broken.

Inactive ingredients:Ethanol 20% USP,

Purified Water.

QUESTIONS

Manufactured by: OHM pharma, Inc, USA.

Distributed by: Privia Naturals, LLC.

9169 W State St #196

Garden City, ID 83714

www.privianaturals.com

Info@privianaturals.com Product of USA.

PACKAGE LABEL

NDC 66343-102-60

RUBIMED

Emvita 15

Homeopathic Medicine For

General Well-being:

Lack of Hope

2.0 fl oz. 59mL 20% Ethanol

PURPOSE

Homeopathic Medicine For

General Well-being:

Lack of Hope